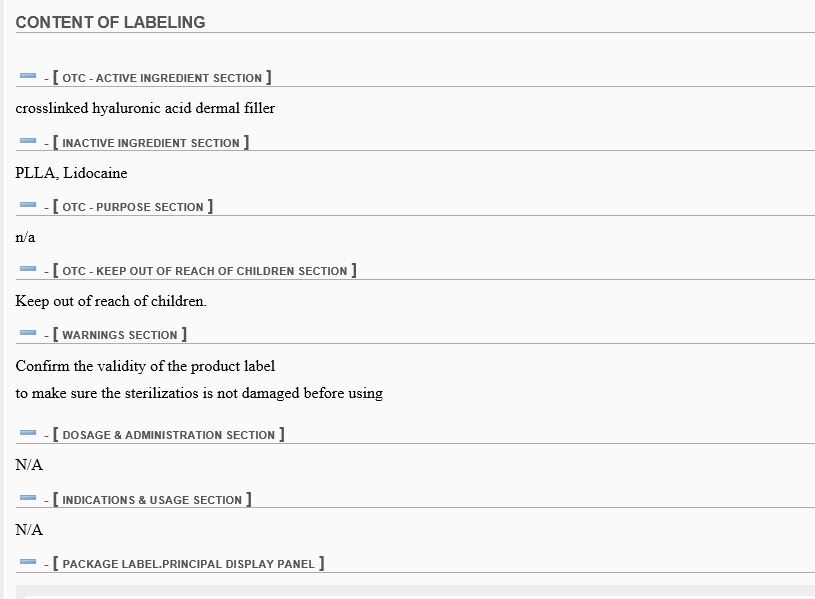 DRUG LABEL: PRO PH Filler
NDC: 71066-0002 | Form: GEL
Manufacturer: PROTOX Inc.
Category: otc | Type: HUMAN OTC DRUG LABEL
Date: 20161115

ACTIVE INGREDIENTS: HYALURONIC ACID 1000 g/20 mL
INACTIVE INGREDIENTS: LIDOCAINE; LACTIC ACID

ACTIVE INGREDIENT

crosslinked hyaluronic acid dermal filler

INACTIVE INGREDIENT

PLLA, Lidocaine

PURPOSE

n/a

Keep out of reach of children.

WARNINGS

Confirm the validity of the product label

to make sure the sterilizatios is not damaged before using

DOSAGE AND ADMINISTRATION

N/A

INDICATIONS AND USAGE

N/A